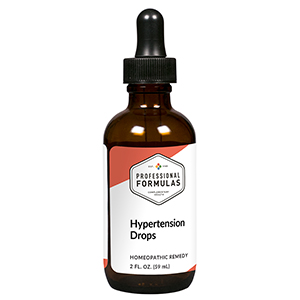 DRUG LABEL: Hypertension Drops
NDC: 63083-2132 | Form: LIQUID
Manufacturer: Professional Complementary Health Formulas
Category: homeopathic | Type: HUMAN OTC DRUG LABEL
Date: 20190815

ACTIVE INGREDIENTS: GARLIC 6 [hp_X]/59 mL; HAWTHORN LEAF WITH FLOWER 6 [hp_X]/59 mL; DIGITALIS 6 [hp_X]/59 mL; NITROGLYCERIN 6 [hp_X]/59 mL; BEEF KIDNEY 6 [hp_X]/59 mL; LYCOPUS VIRGINICUS WHOLE 6 [hp_X]/59 mL; RAUWOLFIA SERPENTINA 6 [hp_X]/59 mL; AVISCUMINE 6 [hp_X]/59 mL; GOLD 12 [hp_X]/59 mL; LYCOPODIUM CLAVATUM SPORE 12 [hp_X]/59 mL; SULFUR 12 [hp_X]/59 mL; BARIUM CHLORIDE DIHYDRATE 12 [hp_X]/59 mL; LEAD 12 [hp_X]/59 mL
INACTIVE INGREDIENTS: ALCOHOL; WATER

C132

ACTIVE INGREDIENTS

Allium sativum 6X
Crataegus oxyacantha 6X
Digitalis purpurea 6X
Glonoinum 6X
Kidney 6X
Lycopus virginicus 6X
Rauwolfia serpentina 6X
Viscum album 6X
Aurum metallicum 12X
Lycopodium clavatum 12X
Sulphur 12X
Baryta muriatica 12X, 30X
Plumbum aceticum 12X, 30X

QUESTIONS

Professional Formulas

PO Box 2034 Lake Oswego, OR 97035

INDICATIONS

For the temporary relief of headache, dizziness, vertigo, or restlessness.*

PURPOSE

*Claims based on traditional homeopathic practice, not accepted medical evidence. Not FDA evaluated.

WARNINGS

In case of overdose, get medical help or contact a poison control center right away.

Keep out of the reach of children.

PREGNANCY OR BREAST FEEDING

If pregnant or breastfeeding, ask a healthcare professional before use.

DIRECTIONS

Place drops under tongue 30 minutes before/after meals. Adults and children 12 years and over: Take 10 drops up to 3 times per day. Consult a physician for use in children under 12 years of age.

OTHER INFORMATION

Tamper resistant. If seal is broken, do not use. After opening, close container tightly and store at room temperature away from heat.

INACTIVE INGREDIENTS

20% ethanol, purified water.

LABEL

Est 1985

Professional Formulas

Complementary Health

Hypertension Drops

Homeopathic Remedy

2 FL. OZ. (59 mL)